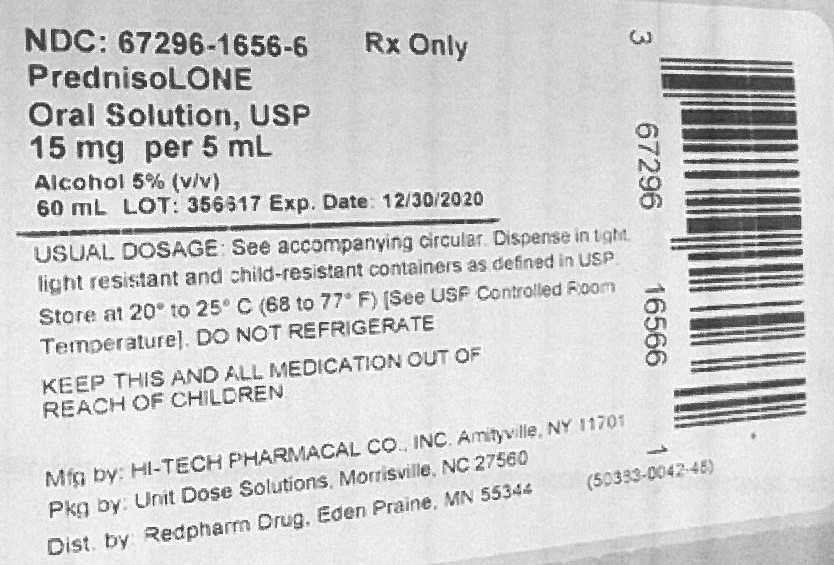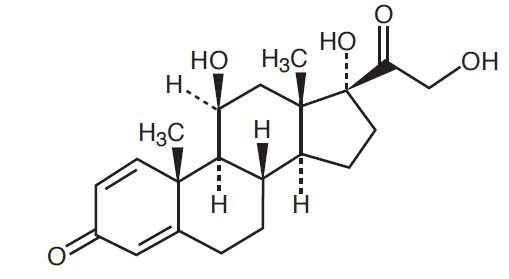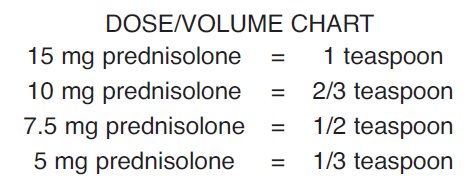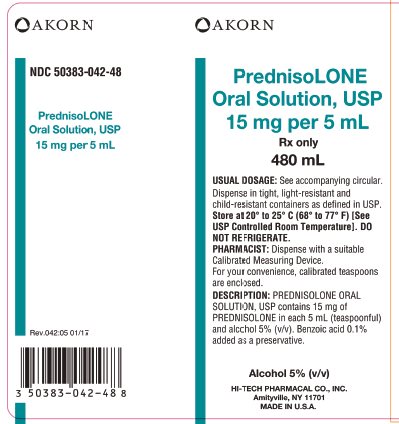 DRUG LABEL: Prednisolone
NDC: 67296-1656 | Form: SOLUTION
Manufacturer: RedPharm Drug, Inc.
Category: prescription | Type: HUMAN PRESCRIPTION DRUG LABEL
Date: 20240809

ACTIVE INGREDIENTS: PREDNISOLONE 15 mg/5 mL
INACTIVE INGREDIENTS: ALCOHOL; ANHYDROUS CITRIC ACID; BENZOIC ACID; CHERRY; EDETATE DISODIUM; FD&C BLUE NO. 1; FD&C RED NO. 40; GLYCERIN; PROPYLENE GLYCOL; SACCHARIN SODIUM; SUCROSE; WATER

PREDNISOLONE ORAL SOLUTION 15 mg per 5 mL

DESCRIPTION

Prednisolone Oral Solution contains prednisolone which is a glucocorticoid. Glucocorticoids are adrenocortical steroids, both naturally occurring and synthetic, which are readily absorbed from the gastrointestinal tract. Prednisolone is a white to practically white, odorless, crystalline powder. It is very slightly soluble in water, soluble in methanol and in dioxane; sparingly soluble in acetone and in alcohol, slightly soluble in chloroform.

The chemical name for Prednisolone is Pregna-1,4 -diene -3, 20 - dione, 11, 17, 21- trihydroxy-,(11β). Its molecular weight is 360.45. The molecular formula is C21H28O5 and the structural formula is:

Prednisolone Oral Solution contains 15 mg of prednisolone in each 5 mL. Benzoic acid, 0.1% is added as a preservative. It also contains alcohol 5%, citric acid, edetate disodium, glycerin, propylene glycol, purified water, sodium saccharin, sucrose, artificial wild cherry flavor, FD&C blue #1 and red #40.

CLINICAL PHARMACOLOGY

Naturally occurring glucocorticoids (hydrocortisone and cortisone), which also have salt-retaining properties, are used as replacement therapy in adrenocortical deficiency states. Their synthetic analogs such as prednisolone are primarily used for their potent anti-inflammatory effects in disorders of many organ systems.

Glucocorticoids such as prednisolone cause profound and varied metabolic effects. In addition, they modify the body’s immune responses to diverse stimuli.

INDICATIONS AND USAGE

PREDNISOLONE Oral Solution is indicated in the following conditions:

1. Endocrine Disorders

Primary or secondary adrenocortical insufficiency (hydrocortisone or cortisone is the first choice: synthetic analogs may be used in conjunction with mineralocorticoids where applicable; in infancy mineralocorticoid supplementation is of particular importance).

1. Congenital adrenal hyperplasia
2. Nonsuppurative thyroiditis
3. Hypercalcemia associated with cancer

2. Rheumatic Disorders

As adjunctive therapy for short-term administration (to tide the patient over an acute episode or exacerbation) in:

1. Psoriatic arthritis
2. Rheumatoid arthritis, including juvenile rheumatoid arthritis (selected cases may require low-dose maintenance therapy)
3. Ankylosing spondylitis
4. Acute and subacute bursitis
5. Acute nonspecific tenosynovitis
6. Acute gouty arthritis
7. Post-traumatic osteoarthritis
8. Synovitis of osteoarthritis
9. Epicondylitis

3. Collagen Diseases

During an exacerbation or as maintenance therapy in selected cases of:

1. Systemic lupus erythematosus
2. Acute rheumatic carditis

4. Dermatologic Diseases

1. Pemphigus
2. Bullous dermatitis herpetiformis
3. Severe erythema multiforme (Stevens-Johnson syndrome)
4. Exfoliative dermatitis
5. Mycosis fungoides
6. Severe psoriasis
7. Severe seborrheic dermatitis

5. Allergic States

Control of severe or incapacitating allergic conditions intractable to adequate trials of conventional treatment:

1. Seasonal or perennial allergic rhinitis
2. Bronchial asthma
3. Contact dermatitis
4. Atopic dermatitis
5. Serum sickness
6. Drug hypersensitivity reactions

6. Ophthalmic Diseases

Severe acute and chronic allergic and inflammatory processes involving the eye and its adnexa such as:

1. Allergic corneal marginal ulcers
2. Herpes zoster ophthalmicus
3. Anterior segment inflammation
4. Diffuse posterior uveitis and choroiditis
5. Sympathetic ophthalmia
6. Allergic conjunctivitis
7. Keratitis
8. Chorioretinitis
9. Optic neuritis
10. Iritis and iridocyclitis

7. Respiratory Diseases

Symptomatic sarcoidosis Loeffler’s syndrome not manageable by other means

1. Berylliosis
2. Fulminating or disseminated pulmonary tuberculosis when used concurrently with appropriate chemotherapy
3. Aspiration pneumonitis

8. Hematologic Disorders

Idiopathic thrombocytopenic purpura in adults

Secondary thrombocytopenia in adults

Acquired (autoimmune) hemolytic anemia

Erythroblastopenia (RBC anemia)

Congenital (erythroid) hypoplastic anemia

9. Neoplastic Diseases

For palliative management of:

1. Acute leukemia of childhood
2. Leukemias and lymphomas in adults

10. Edematous States

To induce a diuresis or remission of proteinuria in the nephrotic syndrome, without uremia, of the idiopathic type or that due to lupus erythematosus.

11. Gastrointestinal Diseases

To tide the patient over a critical period of the disease in:

1. Ulcerative colitis
2. Regional enteritis

12. Miscellaneous

Tuberculous meningitis with subarachnoid block or impending block used concurrently with appropriate antituberculous chemotherapy. Trichinosis with neurologic or myocardial involvement.

In addition to the above indications Prednisolone Oral Solution is indicated for systemic dermatomyositis (polymyositis).

CONTRAINDICATIONS

Systemic fungal infections.

WARNINGS

In patients on corticosteroid therapy subjected to unusual stress, increased dosage of rapidly acting corticosteroids before, during, and after the stressful situation is indicated.

Corticosteroids may mask some signs of infection, and new infections may appear during their use. There may be decreased resistance and inability to localize infection when corticosteroids are used.

Prolonged use of corticosteroids may produce posterior subcapsular cataracts, glaucoma with possible damage to the optic nerves, and may enhance the establishment of secondary ocular infections due to fungi or viruses.

Average and large doses of hydrocortisone or cortisone can cause elevation of blood pressure, salt and water retention, and increased excretion of potassium. These effects are less likely to occur with the synthetic derivatives except when used in large doses. Dietary salt restriction and potassium supplementation may be necessary. All corticosteroids increase calcium excretion.

While on corticosteroid therapy, patients should not be vaccinated against smallpox. Other immunization procedures should not be undertaken in patients who are on corticosteroids, especially on high dose, because of possible hazards of neurological complications and a lack of antibody response.

Persons who are on drugs which suppress the immune system are more susceptible to infections than healthy individuals. Chickenpox and measles, for example, can have a more serious or even fatal course in non-immune children or adults on corticosteroids. In such children or adults who have not had these diseases, particular care should be taken to avoid exposure. How the dose, route and duration of corticosteroid administration affects the risk of developing a disseminated infection is not known. The contribution of the underlying disease and/or prior corticosteroid treatment to the risk is also not known. If exposed to chickenpox, prophylaxis with varicella zoster immune globulin (VZIG) may be indicated. If exposed to measles, prophylaxis with pooled intramuscular immunoglobulin (IG) may be indicated. (See the respective package inserts for complete VZIG and IG prescribing information.) If chickenpox develops, treatment with antiviral agents may be considered.

The use of Prednisolone Oral Solution in active tuberculosis should be restricted to those cases of fulminating or disseminated tuberculosis in which the corticosteroid is used for the management of the disease in conjunction with an appropriate antituberculous regimen.

If corticosteroids are indicated in patients with latent tuberculosis or tuberculin reactivity, close observation is necessary as reactivation of the disease may occur. During prolonged corticosteroid therapy, these patients should receive chemoprophylaxis.

Use in pregnancy: Since adequate human reproduction studies have not been done with corticosteroids, the use of these drugs in pregnancy, nursing mothers or women of childbearing potential requires that the possible benefits of the drug be weighed against the potential hazards to the mother and embryo or fetus. Infants born of mothers who have received substantial doses of corticosteroids during pregnancy should be carefully observed for signs of hypoadrenalism.

PRECAUTIONS

General

Drug-induced secondary adrenocortical insufficiency may be minimized by gradual reduction of dosage. This type of relative insufficiency may persist for months after discontinuation of therapy; therefore, in any situation of stress occurring during that period, hormone therapy should be reinstituted. Since mineralocorticoid secretion may be impaired, salt and/or a mineralocorticoid should be administered concurrently.

There is an enhanced effect of corticosteroids on patients with hypothyroidism and in those with cirrhosis.

Corticosteroids should be used cautiously in patients with ocular herpes simplex because of possible corneal perforation.

The lowest possible dose of corticosteroid should be used to control the condition under treatment, and when reduction in dosage is possible, the reduction should be gradual.

Psychic derangements may appear when corticosteroids are used, ranging from euphoria, insomnia, mood swings, personality changes, and severe depression, to frank psychotic manifestations. Also, existing emotional instability or psychotic tendencies may be aggravated by corticosteroids.

Aspirin should be used cautiously in conjunction with corticosteroids in hypoprothrombinemia.

Steroids should be used with caution in nonspecific ulcerative colitis, if there is a probability of impending perforation, abscess or other pyogenic infections; diverticulitis; fresh intestinal anastomoses; active or latent peptic ulcer; renal insufficiency; hypertension; osteoporosis; and myasthenia gravis.

Growth and development of infants and children on prolonged corticosteroid therapy should be carefully observed.

Information for Patients

Patients who are on immunosuppressant doses of corticosteroids should be warned to avoid exposure to chickenpox or measles. Patients should also be advised that if they are exposed, medical advice should be sought without delay.

ADVERSE REACTIONS

Fluid and Electrolyte Disturbances

1. Sodium retention
2. Fluid retention
3. Congestive heart failure in susceptible patients
4. Potassium loss
5. Hypokalemic alkalosis
6. Hypertension

Musculoskeletal

1. Muscle weakness
2. Steroid myopathy
3. Loss of muscle mass
4. Osteoporosis
5. Vertebral compression fractures
6. Aseptic necrosis of femoral and humeral heads
7. Pathologic fracture of long bones

Gastrointestinal

1. Peptic ulcer with possible perforation and hemorrhage
2. Pancreatitis
3. Abdominal distention
4. Ulcerative esophagitis

Dermatologic

1. Impaired wound healing
2. Thin fragile skin
3. Petechiae and ecchymoses
4. Facial erythema
5. Increased sweating
6. May suppress reactions to skin tests

Neurological

1. Convulsions
2. Increased intracranial pressure with papilledema (pseudo-tumor cerebri) usually after treatment
3. Vertigo
4. Headache

Endocrine

1. Menstrual irregularities
2. Development of Cushingoid state
3. Suppression of growth in children
4. Secondary adrenocortical and pituitary unresponsiveness, particularly in times of stress, as in trauma, surgery or illness
5. Decreased carbohydrate tolerance
6. Manifestations of latent diabetes mellitus
7. Increased requirements for insulin or oral hypoglycemic agents in diabetics

Ophthalmic

1. Posterior subcapsular cataracts
2. Increased intraocular pressure
3. Glaucoma
4. Exophthalmos

Metabolic

1. Negative nitrogen balance due to protein catabolism

To report SUSPECTED ADVERSE REACTIONS, contact Hi-Tech Pharmacal Co., Inc. at 1-800-262-9010 or FDA at 1-800-FDA-1088 or www.fda.gov/medwatch.

DOSAGE AND ADMINISTRATION

Dosage of Prednisolone Oral Solution should be individualized according to the severity of the disease and the response of the patient. For infants and children, the recommended dosage should be governed by the same considerations rather than strict adherence to the ratio indicated by age or body weight.

Hormone therapy is an adjunct to and not a replacement for conventional therapy.

Dosage should be decreased or discontinued gradually when the drug has been administered for more than a few days.

The severity, prognosis, expected duration of the disease, and the reaction of the patient to medication are primary factors in determining dosage.

If a period of spontaneous remission occurs in a chronic condition, treatment should be discontinued.

Blood pressure, body weight, routine laboratory studies, including two-hour postprandial blood glucose and serum potassium, and a chest X-ray should be obtained at regular intervals during prolonged therapy. Upper Gl X-rays are desirable in patients with known or suspected peptic ulcer disease.

The initial dosage of Prednisolone Oral Solution may vary from 5 mg to 60 mg per day depending on the specific disease entity being treated. In situations of less severity lower doses will generally suffice while in selected patients higher initial doses may be required. The initial dosage should be maintained or adjusted until a satisfactory response is noted. If after a reasonable period of time there is a lack of satisfactory clinical response, Prednisolone Oral Solution should be discontinued and the patient transferred to other appropriate therapy. IT SHOULD BE EMPHASIZED THAT DOSAGE REQUIREMENTS ARE VARIABLE AND MUST BE INDIVIDUALIZED ON THE BASIS OF THE DISEASE UNDER TREATMENT AND THE RESPONSE OF THE PATIENT.

After a favorable response is noted, the proper maintenance dosage should be determined by decreasing the initial drug dosage in small decrements at appropriate time intervals until the lowest dosage which will maintain an adequate clinical response is reached. It should be kept in mind that constant monitoring is needed in regard to drug dosage. Included in the situations which may make dosage adjustments necessary are changes in clinical status secondary to remissions or exacerbations in the disease process, the patient’s individual drug responsiveness, and the effect of patient exposure to stressful situations not directly related to the disease entity under treatment. In this latter situation it may be necessary to increase the dosage of Prednisolone Oral Solution for a period of time consistent with the patient’s condition. If after long-term therapy the drug is to be stopped, it is recommended that it be withdrawn gradually rather than abruptly.

HOW SUPPLIED

Prednisolone Oral Solution containing 15 mg of Prednisolone in each 5 mL (teaspoonful) is a red cherry flavored liquid and is supplied in 240 mL bottles and 480 mL bottles.

Pharmacist: Dispense 15 mg/5 mL Prednisolone Oral Solution with suitable calibrated measuring device to assure proper measuring of dose.

Dispense in tight, light-resistant and child-resistant container as defined in USP/NF.

Store at 20° to 25°C (68° to 77°F) [See USP Controlled Room Temperature]. DO NOT REFRIGERATE.

HI-TECH PHARMACAL CO., INC.

Amityville, NY 11701

Rev.042:05 01/17

PACKAGE/LABEL PRINCIPAL DISPLAY PANEL

AKORN

50383-042-48

PrednisoLONE Oral Solution, USP

15 mg per 5 mL

Rx only

480 mL

USUAL DOSAGE: See accompanying circular.

Dispense in tight, light-resistant and child-resistant containers as defined in USP.

Store at 20° to 25°C (68° to 77°F) [See USP Controlled Room Temperature]. DO NOT REFRIGERATE.

PHARMACIST: Dispense with a suitable Calibrated Measuring Device.

For your convenience, calibrated teaspoons are enclosed.

DESCRIPTION: PREDISOLONE ORAL SOLUTION, USP contains 15 mg of PREDNISOLONE in each 5 mL (teaspoonful and alcohol 5% (v/v). Benzoic acid 0.1% added as a preservative.

Alcohol 5% (v/v)

HI-TECH PHARMACAL CO., INC.

Amityville, NY 11701

MADE IN U.S.A.